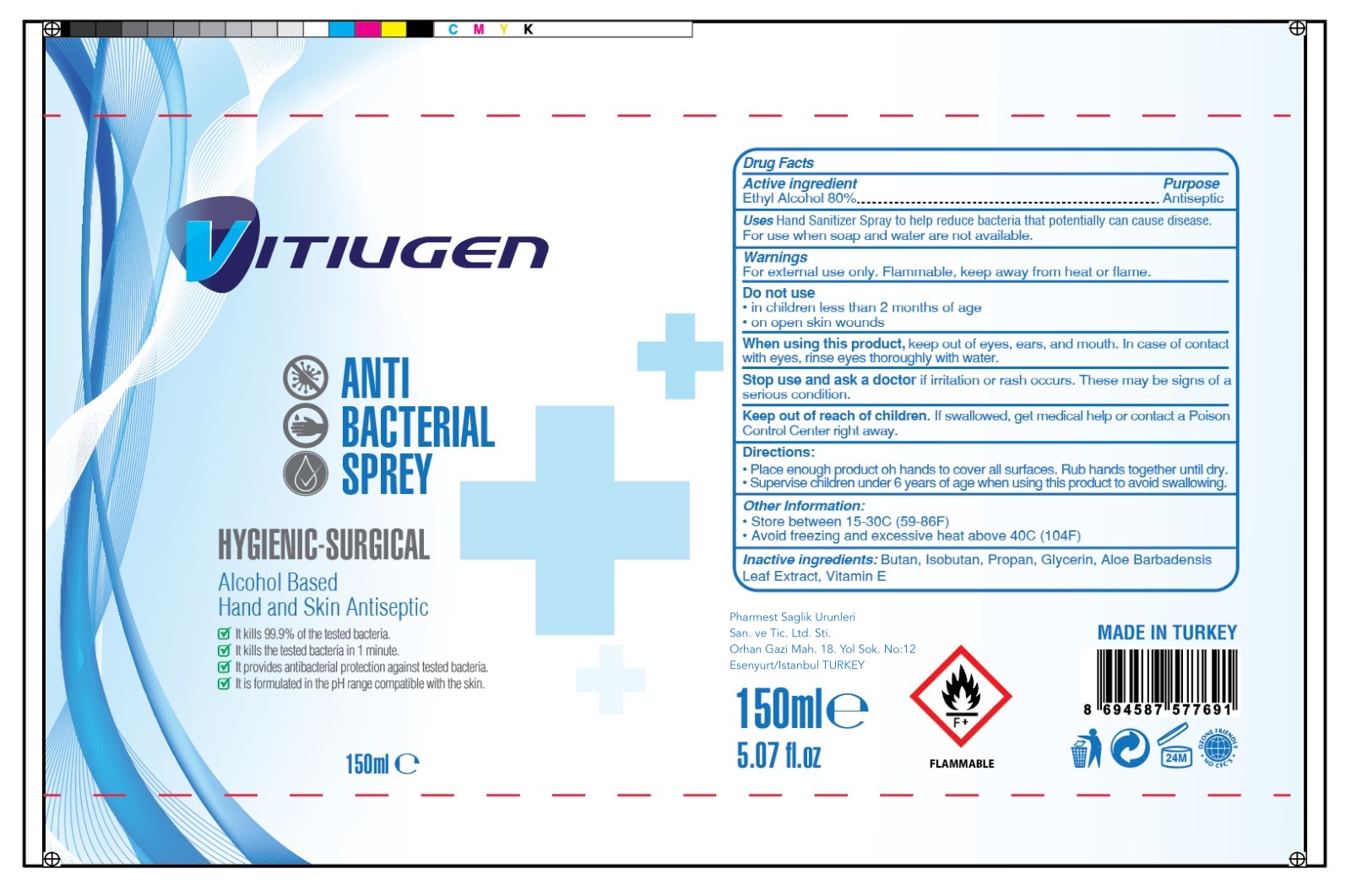 DRUG LABEL: Vitiugen Anti Bacterial Sprey
NDC: 78984-002 | Form: SPRAY
Manufacturer: PHARMEST SAGLIK URUNLERI SANAYI VE TICARET LIMITED SIRKETI
Category: otc | Type: HUMAN OTC DRUG LABEL
Date: 20200622

ACTIVE INGREDIENTS: ALCOHOL 80 mL/100 mL
INACTIVE INGREDIENTS: GLYCERIN; BUTANE; .ALPHA.-TOCOPHEROL; ALOE VERA LEAF; ISOBUTANE; PROPANE

Active Ingredient(s)

Ethyl Alcohol 80%

Purpose

Antiseptic

Use

Hand Sanitizer to help reduce bacteria that potentially can cause disease. For use when soap and water are not available.

Warnings

For external use only. Flammable. Keep away from heat or flame

Do not use

- in children less than 2 months of age
- on open skin wounds

When using this product keep out of eyes, ears, and mouth. In case of contact with eyes, rinse eyes thoroughly with water.

Stop use and ask a doctor if irritation or rash occurs. These may be signs of a serious condition.

Keep out of reach of children. If swallowed, get medical help or contact a Poison Control Center right away.

Directions

- Place enough product on hands to cover all surfaces. Rub hands together until dry.
- Supervise children under 6 years of age when using this product to avoid swallowing.

Other information

- Store between 15-30C (59-86F)
- Avoid freezing and excessive heat above 40C (104F)

Inactive ingredients

Butan, Isobutan, Propan, Glycerin, Aloe Barbadensis Leaf Extract, Vitamin E

Package Label - Principal Display Panel

Vitiugen

Anti Bacterial Sprey

Hygenic-Surgical

Alcohol Based

Hand and Skin Antiseptic

It kills 99.9% of the tested bacteria.

It kills the tested bacteria in 1 minute.

It provides antibacterial protection against tested bacteria.

It is formulated in the pH range compatible with the skin.

Pharmest Saglik Urunleri San. ve Tic. Ltd. Sti.

Orhan Gazi Mah. 18. Yol Sok. No: 12 Esenyurt/Istanbul TURKEY